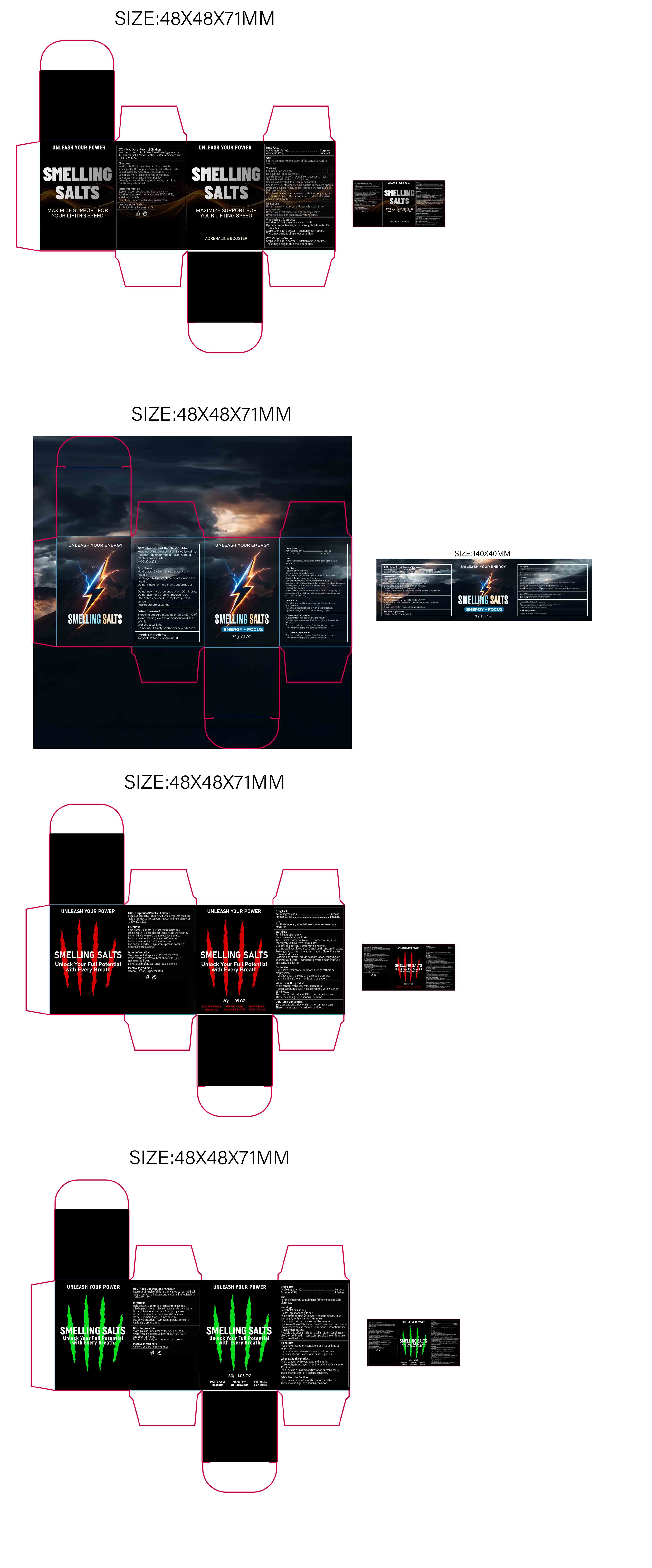 DRUG LABEL: Smelling Salts
NDC: 85839-005 | Form: GRANULE
Manufacturer: Shenzhen Finona Information Technology Co., Ltd
Category: otc | Type: HUMAN OTC DRUG LABEL
Date: 20250810

ACTIVE INGREDIENTS: AMMONIA 0.15 g/1 g
INACTIVE INGREDIENTS: ALCOHOL; COTTON; PEPPERMINT OIL

85839-005 Smelling Salts

ACTIVE INGREDIENT

Ammonia 15%

PURPOSE

Inhalant

INDICATIONS AND USAGE

For the temporary stimulation of the senses to restore alertness.

WARNINGS

For inhalation use only.

Do not ingest or apply to skin.
Avoid direct contact with eyes. lf contact occurs, rinsethoroughly with water for 15 minutes.
Use only as directed. Misuse may be harmful.
Use in a well-ventilated area. Do not use in enclosed spaces.
Prolonged exposure may cause irritation, Discontinue use if discomfort occurs.
Possible side effects include nasal irritation, coughing, or shortness of breath. lf symptoms persist, discontinue use and consult a doctor.

DO NOT USE

It you have respiratory conditions such as asthma oremphysema.
If you have heart disease or high blood pressure.
If you are allergic to ammonia or strong odors.

WHEN USING

Avoid contact with eyes, ears, and mouth.
lf product gets into eyes, rinse thoroughly with water for 15 minutes.
Stop use and ask a doctor ifirritation or rash occurs.
These may be signs of a serious condition.

Keep out of reach of children. lfswallowed, get medical
help or contact a Poison Control centerimmediately at
1-800-222-1222

DOSAGE AND ADMINISTRATION

Hold bottle 10-15 cm (4-6 inches) from nostrils.
Inhale gently. Do not place directly inside the nostrils.
Do not inhale for more than 2 seconds per use.
Do not use more than once every 60 minutes.
Do not use more than 10 times per day.
Use only as needed. lfsymptoms persist, consult ahealthcare professional

INACTIVE INGREDIENT

Alcohol
Cotton
Peppermint Oil